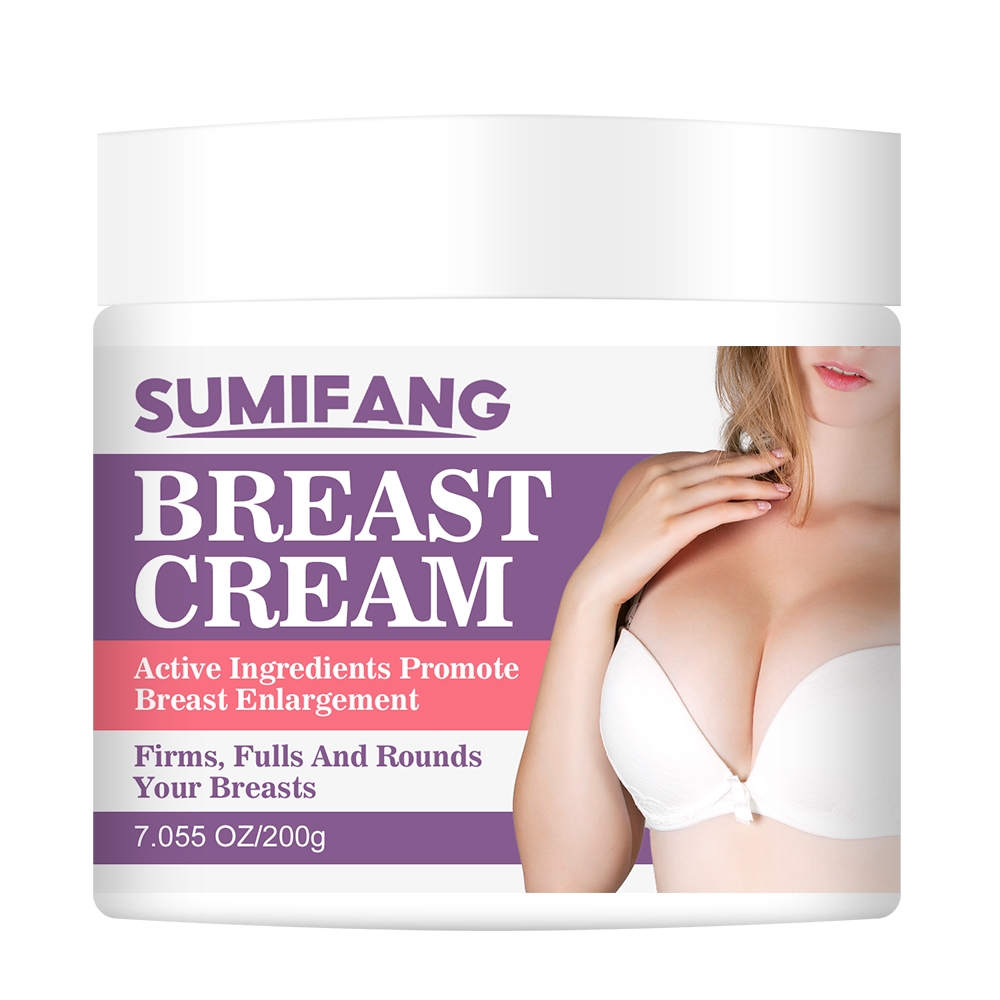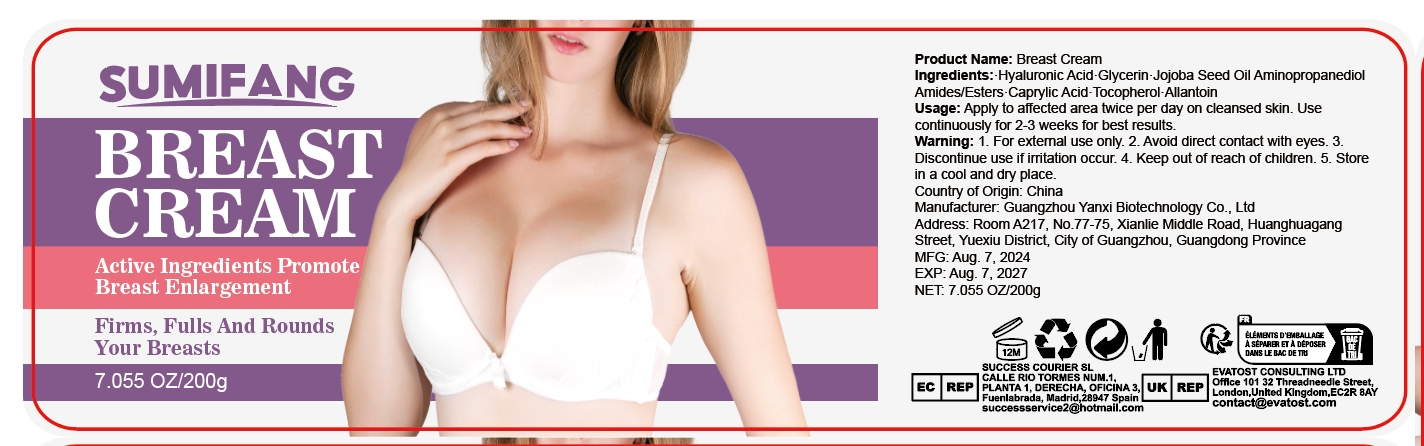 DRUG LABEL: BREASTCREAM
NDC: 84025-129 | Form: CREAM
Manufacturer: Guangzhou Yanxi Biotechnology Co.. Ltd
Category: otc | Type: HUMAN OTC DRUG LABEL
Date: 20240812

ACTIVE INGREDIENTS: CAPRYLIC ACID 3 mg/200 g; GLYCERIN 5 mg/200 g
INACTIVE INGREDIENTS: WATER

DOSAGE AND ADMINISTRATION

Cream for massaging and nourishing the breast skin

WARNINGS

keep out of children

INACTIVE INGREDIENT

Aqua

INDICATIONS AND USAGE

Apply to affected area twice per day on cleansed skin

Keep out of children

PURPOSE

For moisturizing and firming breast skin